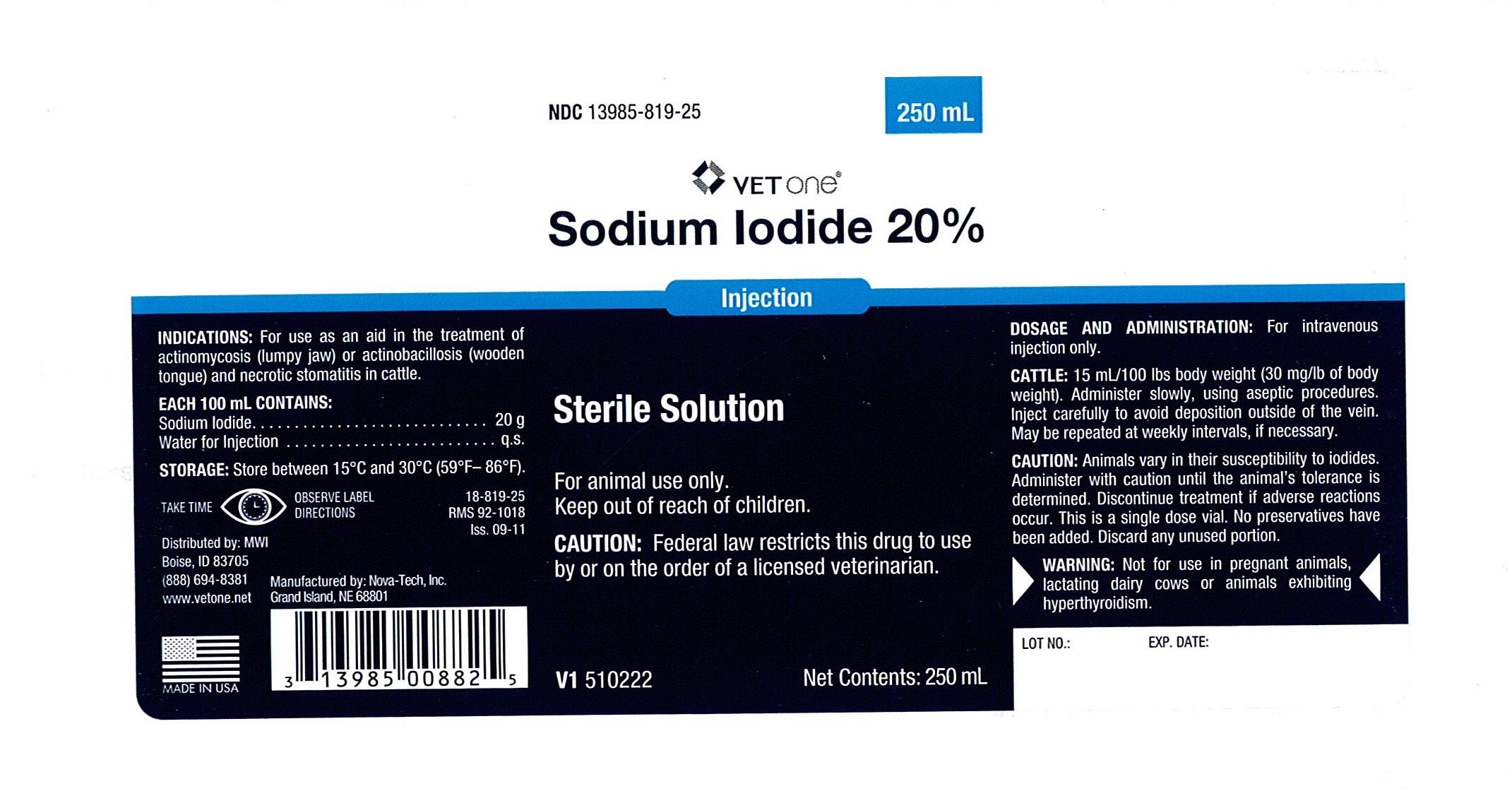 DRUG LABEL: Sodium Iodide
NDC: 13985-819 | Form: INJECTION, SOLUTION
Manufacturer: MWI (VetOne)
Category: animal | Type: PRESCRIPTION ANIMAL DRUG LABEL
Date: 20111014

ACTIVE INGREDIENTS: Sodium Iodide 20 g/100 mL

Sodium Iodide 20%

INDICATIONS

For use as an aid in the treatment of actinomycosis (lump jaw) or actinobacillosis (wooden tongue) and necrotic stomatitis in cattle.

EACH 100 mL CONTAINS

Sodium Iodide .............................. 20 g

Water for Injection ......................... q.s.

STORAGE

Store between 15 degree C and 30 degree C (59 degree F - 85 degree F).

SAFE HANDLING WARNING

Take time. Observe label directions

VETERINARY INDICATIONS

For animal use only.

Keep out reach of children

CAUTION

Federal law restricts this drug to use by or on the order of a licensed veterinarian.

DOSAGE AND ADMINISTRATION

For intravenous injection only.

CATTLE: 15 mL/100 lb body weight (30 mg/lb of body weight). Administer slowly, using aseptic procedures. Inject carefully to avoid deposition outside of the vein. May be repeated at weekly intervals, if necessary.

CAUTION

Animals vary in their susceptibility to iodides. Administer with caution until the animal's tolerance is determined. Discontinue treatment if adverse reactions occur. This is a single dose vial. No preservatives have been added. Discard any unused portion.

WARNING

Not for use in pregnant animals, lactating dairy cows or animals exhibiting hyperthyroidism.

PACKAGE LABEL

Enter section text here